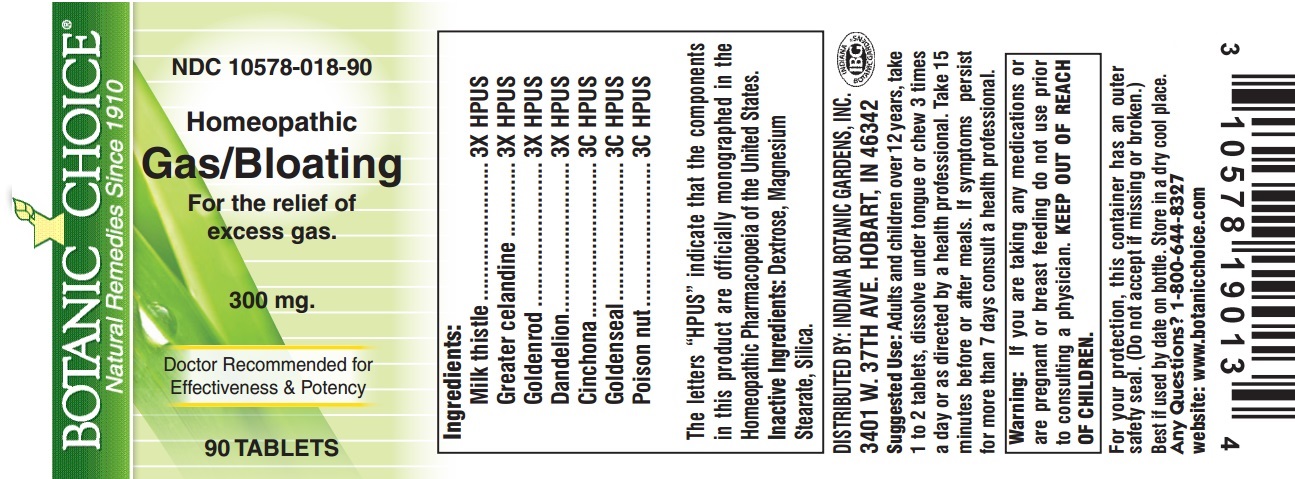 DRUG LABEL: Homeopathic Gas Relief Formula
NDC: 10578-018 | Form: TABLET
Manufacturer: Indiana Botanic Gardens
Category: homeopathic | Type: HUMAN OTC DRUG LABEL
Date: 20150318

ACTIVE INGREDIENTS: MILK THISTLE 3 [hp_X]/1 1; CHELIDONIUM MAJUS 3 [hp_X]/1 1; SOLIDAGO VIRGAUREA FLOWERING TOP 3 [hp_X]/1 1; TARAXACUM OFFICINALE 3 [hp_X]/1 1; CINCHONA OFFICINALIS BARK 3 [hp_C]/1 1; GOLDENSEAL 3 [hp_C]/1 1; STRYCHNOS NUX-VOMICA SEED 3 [hp_C]/1 1
INACTIVE INGREDIENTS: DEXTROSE; MAGNESIUM STEARATE; SILICON DIOXIDE

Homeopathic Gas Relief Formula

Ingredients:

Milk thistle ........................3X HPUS

Greater celandine .............3X HPUS

Goldenrod .........................3X HPUS

Dandelion ..........................3X HPUS

Cinchona ...........................3C HPUS

Goldenseal ........................3C HPUS

Poison nut .........................3C HPUS

The letters "HPUS" indicate that the components in this product are officially monographed in the Homeopathic Pharmacopoeia of the United States.

Inactive Ingredients:

Dextrose, Magnesium Stearate, Silica.

DISTRIBUTED BY: INDIANA BOTANIC GARDENS, INC.

3401 W. 37TH AVE. HOBART, IN 46342

Suggested Use:

Adults and children over 12 years, take 1 to 2 tablets, dissolve under tongue or chew 3 times a day or as directed by a health professional. Take 15 minutes before or after meals.

STOP USE

If symptoms persist for more than 7 days consult a health professional.

Warning:

If you are taking any medications or are pregnant or breast feeding do not use prior to consulting a physician.

KEEP OUT OF REACH OF CHILDREN.

For your protection, this container has an outer safety seal. (Do not accept if missing or broken.)

Best if used by date on bottle. Store in a dry cool place.

Any Questions?

1-800-644-8327

website: www.botanicchoice.com

INDICATIONS AND USAGE

For the relief of excess gas.

PURPOSE

For the relief of excess gas.

Botanic Choice

Natural Remedies Since 1910

NDC 10578-018-90

Homeopathic Gas/Bloating

For the relief of excess gas.

300 mg.

Doctor Recommended for Effectiveness & Potency

90 TABLETS